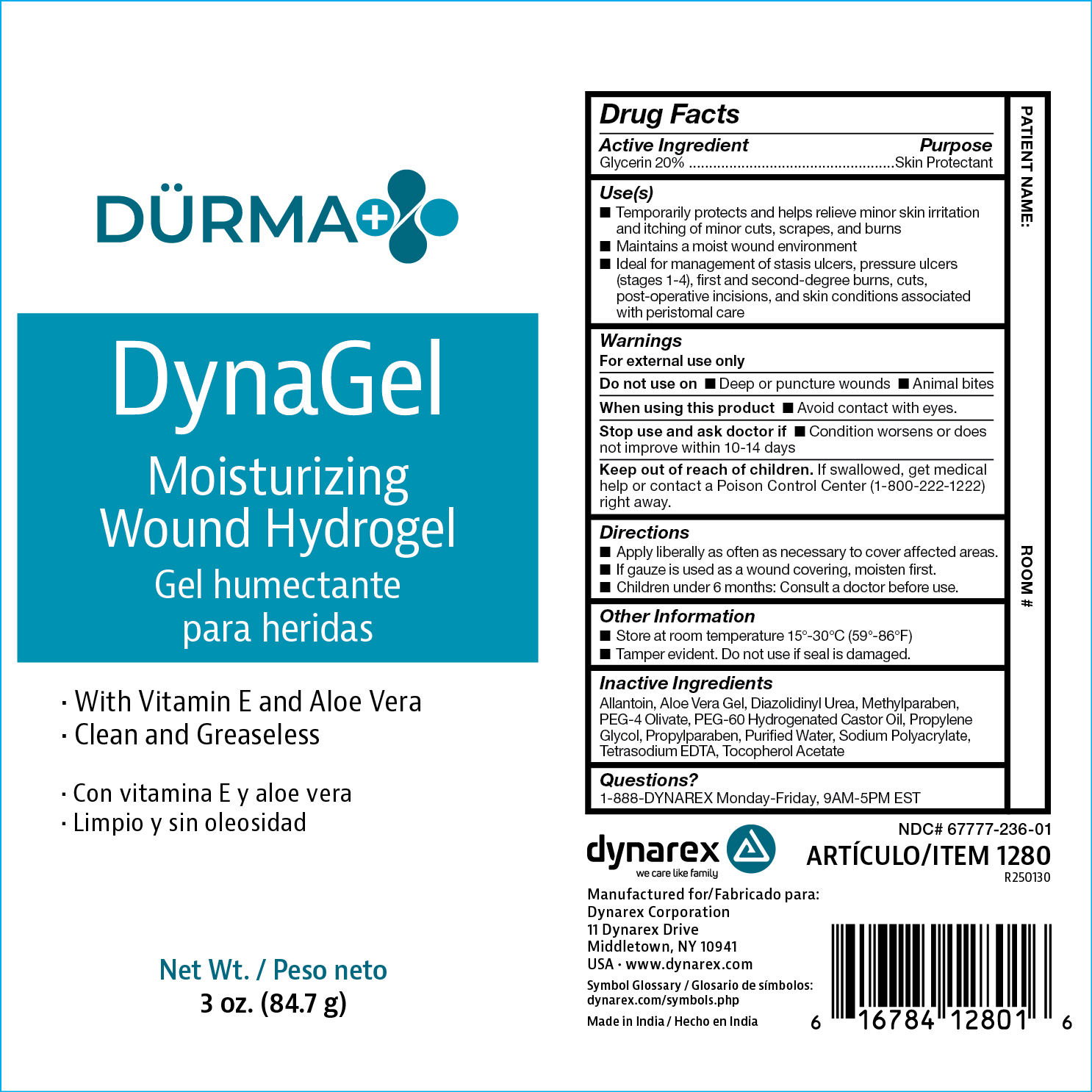 DRUG LABEL: Durma DynaGel
NDC: 67777-236 | Form: GEL
Manufacturer: Dynarex Corporation
Category: otc | Type: HUMAN OTC DRUG LABEL
Date: 20250807

ACTIVE INGREDIENTS: GLYCERIN 20 g/100 g
INACTIVE INGREDIENTS: DIAZOLIDINYL UREA; EDETATE SODIUM; METHYLPARABEN; POLYOXYL 60 HYDROGENATED CASTOR OIL; PROPYLPARABEN; WATER; ALPHA-TOCOPHEROL ACETATE; ALOE VERA LEAF; ALLANTOIN; SODIUM POLYACRYLATE (8000 MW); PROPYLENE GLYCOL

1280 Durma DynaGel

Active Ingredient

Glycerin 20%

Purpose

Skin Protectant

Use(s)

• Temporarily protects and helps relieve minor skin irritation and itching of minor cute, scrapes, and burns

• Maintains a moist wound environment

• Ideal for management of stasis ulcers, pressure ulcers (stage 1-4), first second-degree burns, cuts, post-operative incicions, and skin conditions associated with peristomal care

Warnings

For External Use Only

Do not use on

• deep or puncture wounds • Animal bites

When using this product

• Avoid contact with eyes.

Stop use and ask a doctor if

• Condition worsens or does not improve withing 10-14 days

Keep out of reach of children.

If swallowed, get medical help or contact a Poison Control Center (1-800-222-1222) right away.

Directions

• Apply liberally as often as necessary to cover affected areas.

• If gauze is used, as a wound covering, moisten first.

• Children under 6 months: Consult a doctor before use.

Other Information

• Store at room temperature 15° - 30ºC (59° - 86°F) • Tamper evident. Do not use if seal is damaged.

Inactive Ingredients

Allantoin, Aloe Vera Gel, Diazolidinyl Urea, Methylparaben, PEG-4 Olivate, PEG-60 Hydrogenated Castor Oil, Propylene Glycol, Propylparaben, Purified Water, Sodium Polyacrylate, Tetrasodium EDTA, Tocopherol Acetate

Questions?

• 1-888-DYNAREX Monday - Friday, 9AM - 5PM EST.

Label

1280 Durma DynaGel